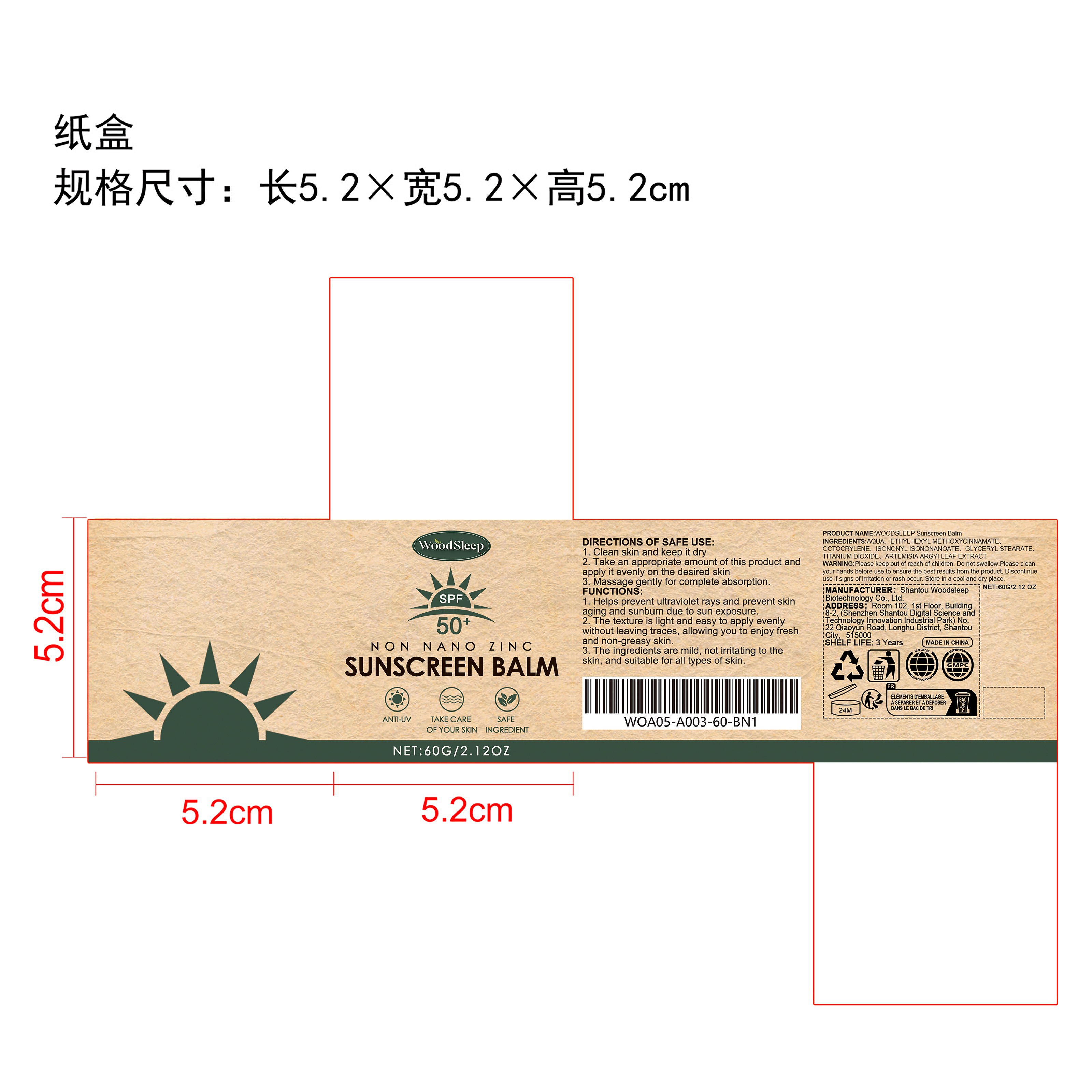 DRUG LABEL: WOODSLEEP Sunscreen Balm
NDC: 85053-004 | Form: CREAM
Manufacturer: Shantou Woodsleep Biotechnology Co., Ltd.
Category: otc | Type: HUMAN OTC DRUG LABEL
Date: 20251213

ACTIVE INGREDIENTS: ARTEMISIA ARGYI LEAF 0.012 mg/60 mg
INACTIVE INGREDIENTS: TITANIUM DIOXIDE 0.6 mg/60 mg; GLYCERYL STEARATE 0.9 mg/60 mg; OCTOCRYLENE 3 mg/60 mg; ETHYLHEXYL METHOXYCINNAMATE 3 mg/60 mg; ISONONYL ISONONANOATE 2.4 mg/60 mg; AQUA 50.088 mg/60 mg

ACTIVE INGREDIENT

ARTEMISIA ARGYI LEAF EXTRACT

PURPOSE

1. Helps prevent ultraviolet rays and prevent skin aging and sunburn due to sun exposure.

2. The texture is light and easy to apply evenly without leaving traces, allowing you to enjoy fresh and non-greasy skin.

3. The ingredients are mild, not irritating to the skin, and suitable for all types of skin.

WHEN USING

1. Clean skin and keep it dry

2. Take an appropriate amount of this product and apply it evenly on the desired skin

3. Massage gently for complete absorption.

WARNINGS

Please keep out of reach of children. Do not swallow.Please clean your hands before use to ensure the best results from the product. Discontinue use if signs of irritation or rash occur. Store in a cool and dry place.

DO NOT USE

Discontinue use if signs of irritation or rash occur.

STOP USE

Discontinue use if signs of irritation or rash occur.

KEEP OUT OF REACH OF CHILDREN

Please keep out of reach of children. Do not swallow.

STORAGE AND HANDLING

Store in a cool and dry place.

INACTIVE INGREDIENT

AQUA、ETHYLHEXYL METHOXYCINNAMATE、OCTOCRYLENE、ISONONYL ISONONANOATE、GLYCERYL STEARATE、TITANIUM DIOXIDE

DOSAGE AND ADMINISTRATION

1. Clean skin and keep it dry

2. Take an appropriate amount of this product and apply it evenly on the desired skin

3. Massage gently for complete absorption.

INDICATIONS AND USAGE

1. Clean skin and keep it dry

2. Take an appropriate amount of this product and apply it evenly on the desired skin

3. Massage gently for complete absorption.